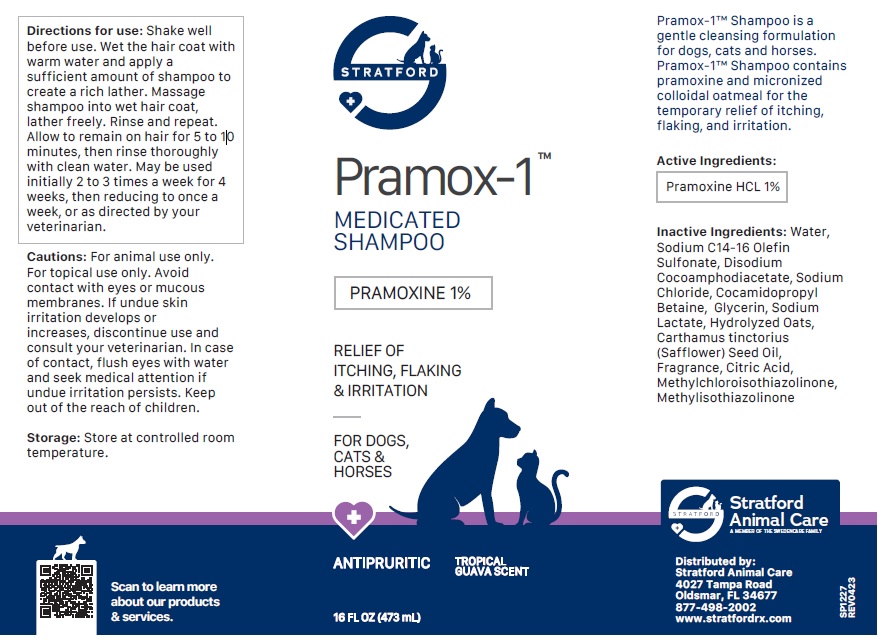 DRUG LABEL: Pramox-1
NDC: 86069-109 | Form: SHAMPOO
Manufacturer: Stratford Care Usa, Inc.
Category: animal | Type: OTC ANIMAL DRUG LABEL
Date: 20250425

ACTIVE INGREDIENTS: PRAMOXINE HYDROCHLORIDE 1 g/100 mL
INACTIVE INGREDIENTS: WATER; SODIUM C14-16 OLEFIN SULFONATE; DISODIUM COCOAMPHODIACETATE; SODIUM CHLORIDE; COCAMIDOPROPYL BETAINE; GLYCERIN; SODIUM LACTATE; OATMEAL; SAFFLOWER OIL; CITRIC ACID MONOHYDRATE; METHYLCHLOROISOTHIAZOLINONE; METHYLISOTHIAZOLINONE

Pramox-1™ Shampoo

Active Ingredients:

Pramoxine HCL 1%

PURPOSE

ANTIPRURITIC

INDICATIONS AND USAGE

Pramox-1™ Shampoo is a gentle cleansing formulation for dogs, cats and horses. Pramox-1™ Shampoo contains pramoxine and micronized colloidal oatmeal for the temporary relief of itching, flaking, and irritation.

INACTIVE INGREDIENT

Inactive Ingredients: Water, Sodium C14-16 Olefin Sulfonate, Disodium Cocoamphodiacetate, Sodium Chloride, Cocamidopropyl Betaine, Glycerin, Sodium Lactate, Hydrolyzed Oats, Carthamus tinctorius (Safflower) Seed Oil, Fragrance, Citric Acid, Methylchloroisothiazolinone, Methylisothiazolinone

DOSAGE AND ADMINISTRATION

Directions for use: Shake well before use. Wet the hair coat with warm water and apply a sufficient amount of shampoo to create a rich lather. Massage shampoo into wet hair coat, lather freely. Rinse and repeat. Allow to remain on hair for 5 to 10 minutes, then rinse thoroughly with clean water. May be used initially 2 to 3 times a week for 4 weeks, then reducing to once a week, or as directed by your veterinarian.

PRECAUTIONS

Cautions: For animal use only. For topical use only. Avoid contact with eyes or mucous membranes. If undue skin irritation develops or increases, discontinue use and consult your veterinarian. In case of contact, flush eyes with water and seek medical attention if undue irritation persists. Keep out of the reach of children.

Storage: Store at controlled room temperature.

MEDICATED SHAMPOO

RELIEF OF ITCHING, FLAKING & IRRITATION

FOR DOGS, CATS & HORSES

TROPICAL GUAVA SCENT

Stratford Animal Care
A MEMBER OF THE SWEDENCARE FAMILY

Distributed by:
Stratford Animal Care
4027 Tampa Road
Oldsmar, FL 34677
877-498-2002
www.stratfordrx.com